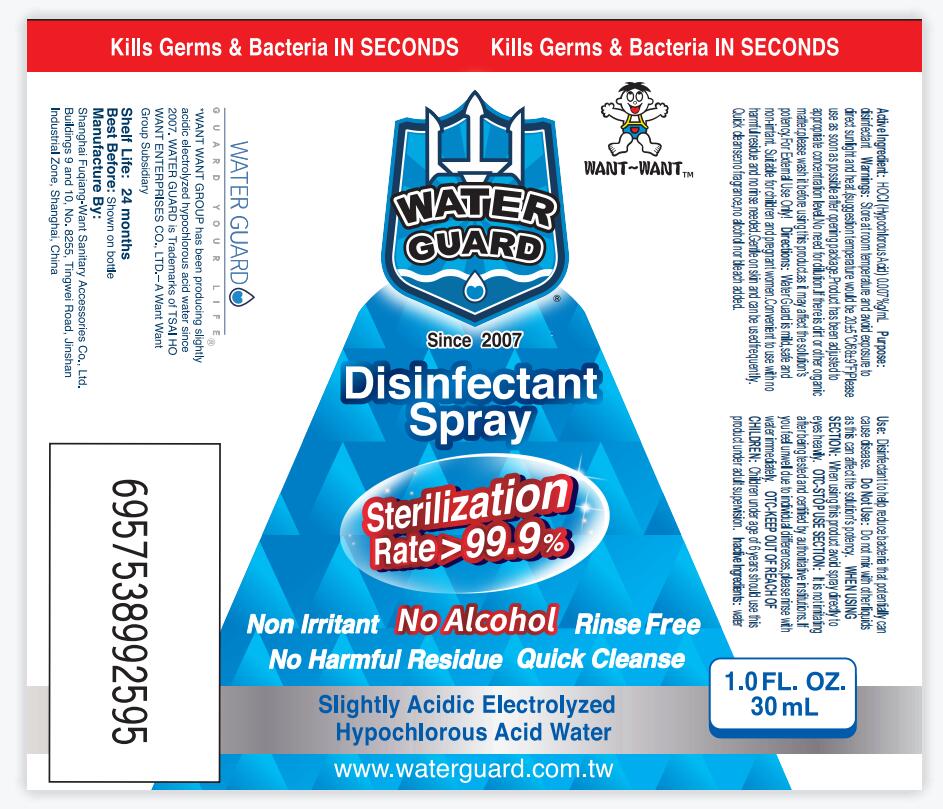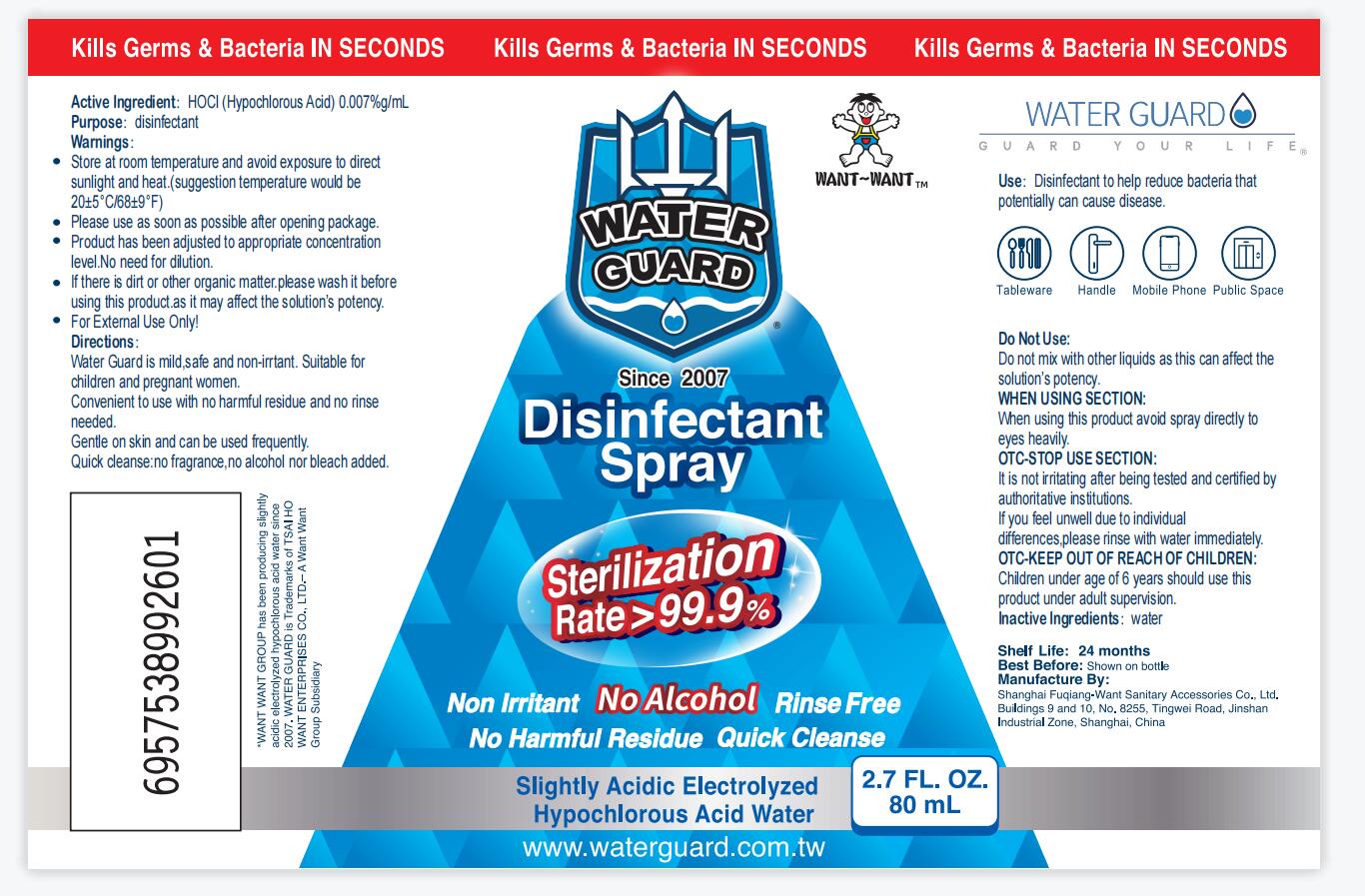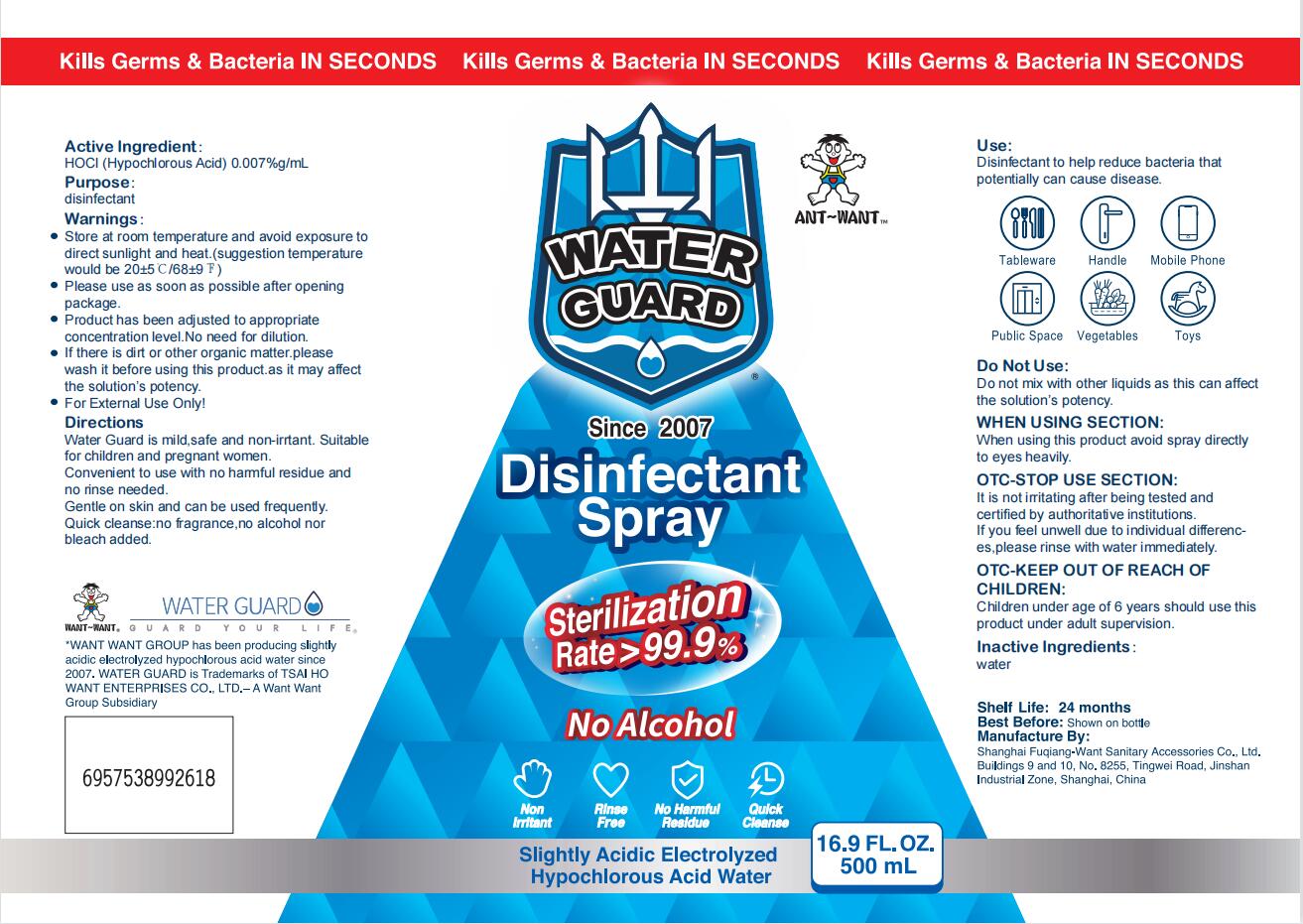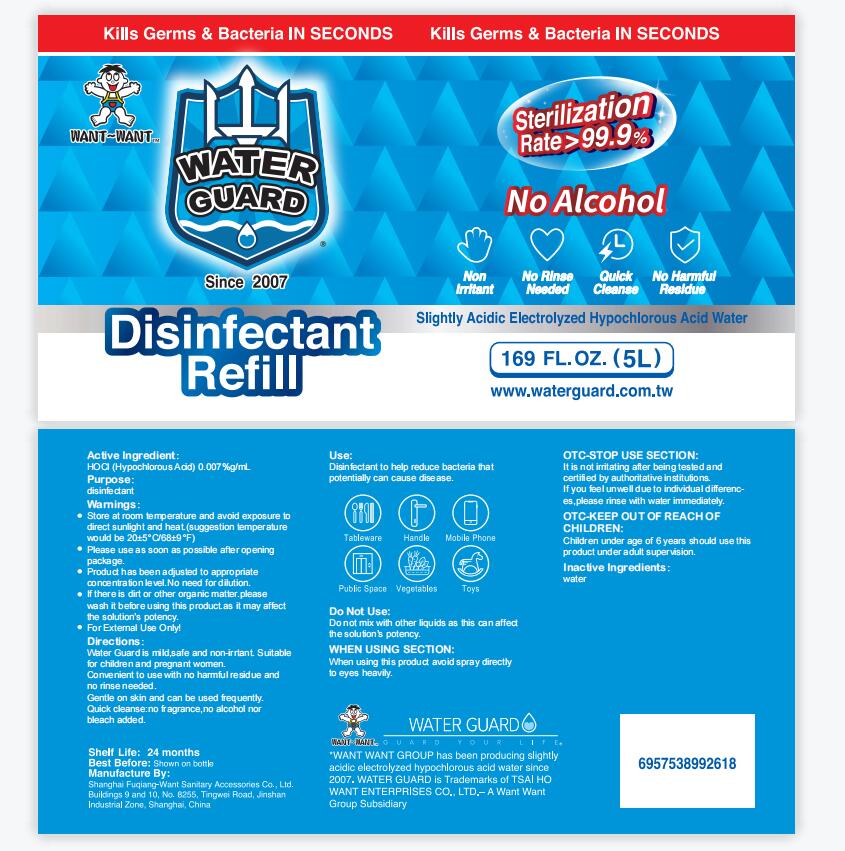 DRUG LABEL: Water Guard Slightly Acidic Electrolyzed Hypochlorous Acid Water Disinfectant
NDC: 82750-001 | Form: SPRAY
Manufacturer: SHANGHAI FUQIANG-WANT SANITARY ACCESSORIES CO., LTD
Category: otc | Type: HUMAN OTC DRUG LABEL
Date: 20220520

ACTIVE INGREDIENTS: HYPOCHLOROUS ACID 0.008 mg/100 mL
INACTIVE INGREDIENTS: WATER

82750-001

Active Ingredient

Hypochlorous Acid 0.007%

Purpose

disinfectant

Use

Disinfectant to help reduce bacteria that potentially can cause disease.

Warnings

Store at room temperature and avoid exposure to direct sunlight and heat.(suggestion temperature would be 20±5℃/68±9℉).
Please use as soon as possible after opening package.
Product has been adjusted to appropriate concentration level.No need for dilution.
If there is dirt or other organic matter.please wash it before using this product.as it may affect the solution’s potency.
For External Use Only!

Do Not Use

Do not mix with other liquids as this can affect the solution’s potency.

WHEN USING SECTION

When using this product avoid spray directly to eyes heavily.

OTC-STOP USE SECTION

It is not irritating after being tested and certified by authoritative institutions.
If you feel unwell due to individual differences,please rinse with water immediately.

OTC-KEEP OUT OF REACH OF CHILDREN

Children under age of 6 years should use this product under adult supervision.

Directions

Water Guard is mild,safe and non-irrtant. Suitable for children and pregnant women.
Convenient to use with no harmful residue and no rinse needed.
Gentle on skin and can be used frequently.
Quick cleanse:no fragrance,no alcohol nor bleach added.

Inactive Ingredients

water